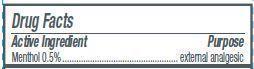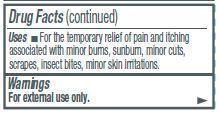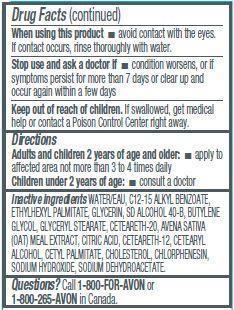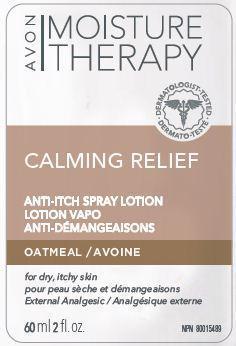 DRUG LABEL: Moisture Therapy
NDC: 10096-0146 | Form: SPRAY
Manufacturer: Avon Products, Inc.
Category: otc | Type: HUMAN OTC DRUG LABEL
Date: 20141002

ACTIVE INGREDIENTS: Menthol 5 mg/1 mL

Active ingredient
Menthol 0.5 %......

Purpose
.........External Analgesic

Uses
For the temporary relief of pain and itching associated with minor burns, sunburn, minor cuts, scrapes, insect bites, minor skin irritations.

Warnings
For external use only

When using this product

- avoid contact with the eyes. If contact occurs, rinse thoroughly with water.

Stop use and ask a doctor if

- condition worsens, or if symptoms persist for more than 7 days or clear up and occur again within a few days

Keep out of reach of children. If swallowed, get medical help or contact a Poison Control Center right away

Directions
Adults and children 2 years of age and older:

- apply to affected area not more than 3 to 4 times daily

Children under 2 years of age:

- consult a doctor before use

Inactive Ingredients:
WATER/EAU, C12-15 ALKYL BENZOATE, ETHYLHEXYL PALMITATE, GLYCERIN, SD ALCOHOL 40-B, BUTYLENE GLYCOL, GLYCERYL STEARATE,
CETEARETH-20, AVENA SATIVA (OAT) MEAL EXTRACT, CITRIC ACID, CETEARETH-12, CETEARYL ALCOHOL, CETYL PALMITATE, CHOLESTEROL, CHLORPHENESIN, SODIUM HYDROXIDE, SODIUM DEHYDROACETATE.

Questions?
Call 1-800-FOR-AVON or 1-800-265-AVON in Canada.